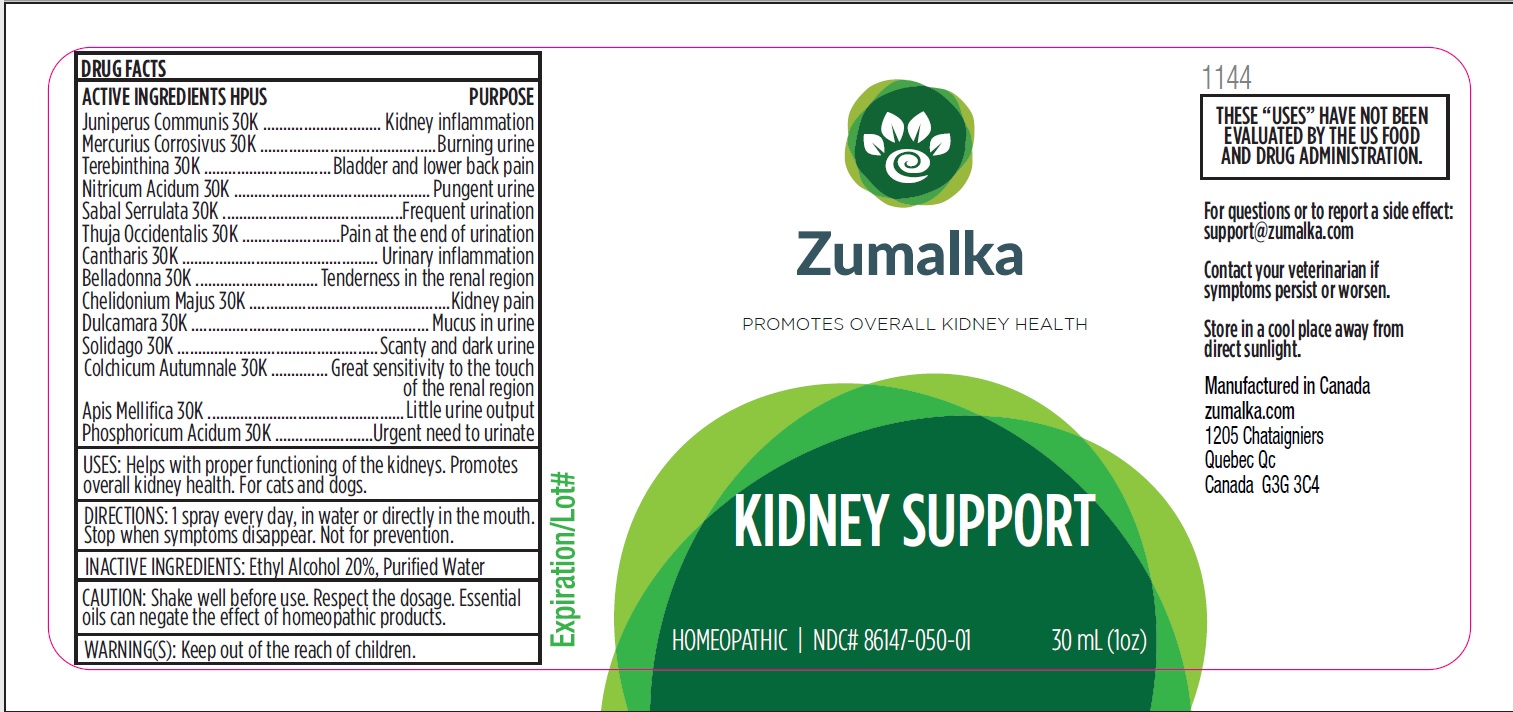 DRUG LABEL: KIDNEY SUPPORT
NDC: 86147-050 | Form: LIQUID
Manufacturer: Groupe Cyrenne Inc.
Category: homeopathic | Type: OTC ANIMAL DRUG LABEL
Date: 20251120

ACTIVE INGREDIENTS: JUNIPER BERRY 30 [kp_C]/30 mL; MERCURIC CHLORIDE 30 [kp_C]/30 mL; TURPENTINE OIL 30 [kp_C]/30 mL; NITRIC ACID 30 [kp_C]/30 mL; SAW PALMETTO 30 [kp_C]/30 mL; THUJA OCCIDENTALIS LEAFY TWIG 30 [kp_C]/30 mL; SOLIDAGO VIRGAUREA FLOWERING TOP 30 [kp_C]/30 mL; LYTTA VESICATORIA 30 [kp_C]/30 mL; ATROPA BELLADONNA 30 [kp_C]/30 mL; CHELIDONIUM MAJUS WHOLE 30 [kp_C]/30 mL; SOLANUM DULCAMARA TOP 30 [kp_C]/30 mL; COLCHICUM AUTUMNALE FLOWER 30 [kp_C]/30 mL; APIS MELLIFERA 30 [kp_C]/30 mL; PHOSPHORIC ACID 30 [kp_C]/30 mL
INACTIVE INGREDIENTS: ALCOHOL; WATER

Active ingredients Purpose

Juniperus Communis 30k Kidney inflammation

Mercurius Corrosivus 30k Burning urine

Terebinthina 30k Bladder and lower back pain

Nitricum Acidum 30k Pungent urine

Sabal Serrulata 30k Frequent urination

Thuja Occidentalis 30k Pain at the end of urination

Cantharis 30k Urinary inflammation

Belladonna 30k Tenderness in the renal region

Chelidonium Majus 30k Kidney pain

Dulcamara 30k Mucus in urine

Solidago 30k Scanty and dark urine

Colchicum Autumnale 30k Great sensitivity to the touch of the renal region

Apis Mellifica 30k Little urine output

Phosphoricum Acidum 30k Urgent need to urinate

Uses

Helps with proper functioning of the kidneys. Promotes overall kidney health. For cats and dogs only.

Warnings

Keep out of reach of children.

Direction

1 spray every day, in water or directly in the mouth. Not for prevention.

Inactive ingredients

Ethyl alcohol 20%, purified water

Cautions

Shake well before use. Respect the dosage. Essential oils can negate the effects of homeopathic products. Store in a cool place away from direct sunlight.